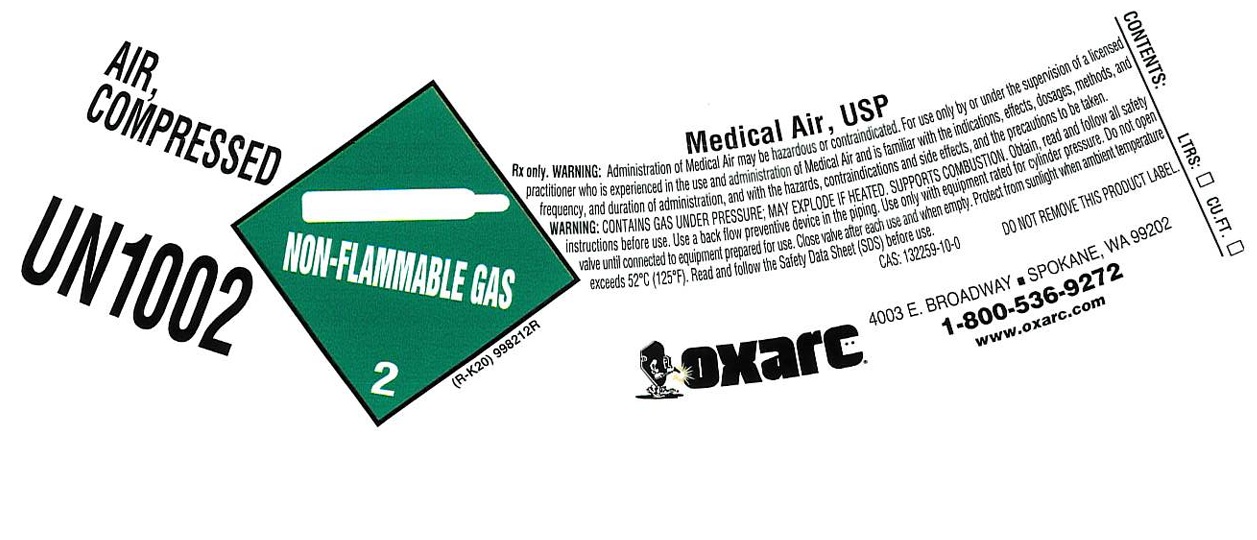 DRUG LABEL: Air
NDC: 34057-006 | Form: GAS
Manufacturer: Oxarc, LLC
Category: prescription | Type: HUMAN PRESCRIPTION DRUG LABEL
Date: 20251125

ACTIVE INGREDIENTS: AIR 1000 mL/1 L

air

PACKAGE LABEL

AIR, COMPRESSED

UN1002

Medical Air, USP

Rx only. WARNING: Administration of Medical Air may be hazardous or contraindicated. For use only by or under the supervision of a licensed practitioner who is experienced in the use and administration of Medical Air and is familiar with the indications, effects, dosages, methods, and frequency, and duration of administration, and with the hazards, contraindications and side effects, and the precautions to be taken.

WARNING: CONTAINS GAS UNDER PRESSURE; MAY EXPLODE IF HEATED. SUPPORTS COMBUSTION. Obtain, read and follow all safety instructions before use. Use a back flow preventive device in the piping. Use only with equipment rated for cylinder pressure. Do not open valve until connected to equipment prepared for use. Close valve after each use and when empty. Protect from sunlight when ambient temperature exceeds 52 C (125 F). Read and follow the Safety Data Sheet (SDS) before use.

CAS: 132259-10-0 DO NOT REMOVE THIS PRODUCT LABEL.

OXARC

4003 E. BROADWAY SPOKANE, WA 99202

1-800-536-9272

www.oxarc.com

CONTENTS: LTRS: CU.FT.